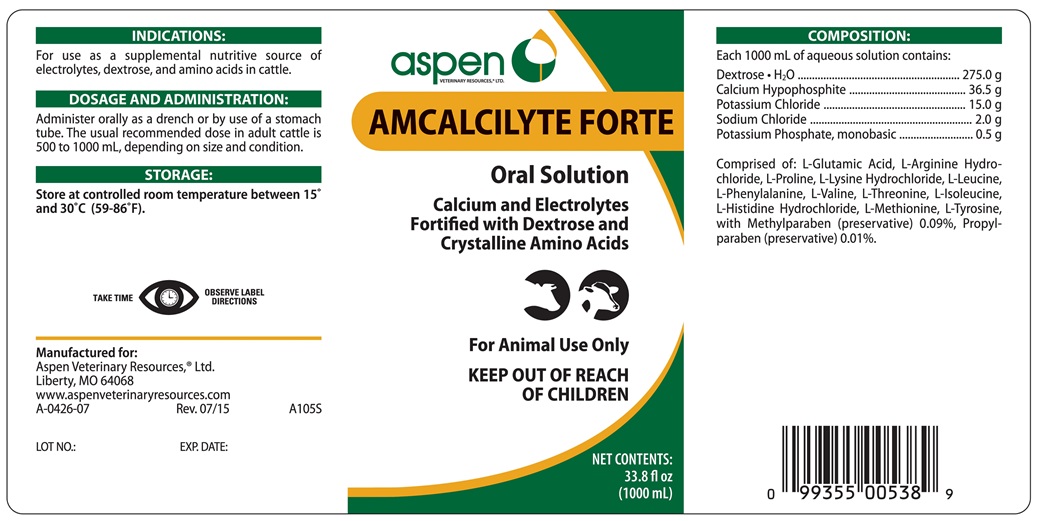 DRUG LABEL: AMCALCILYTE 
NDC: 46066-242 | Form: SOLUTION
Manufacturer: Aspen Veterinary Resources, Ltd.
Category: animal | Type: OTC ANIMAL DRUG LABEL
Date: 20170626

ACTIVE INGREDIENTS: CALCIUM HYPOPHOSPHITE 36.5 g/1000 mL; DEXTROSE MONOHYDRATE 275 g/1000 mL; POTASSIUM CHLORIDE 15 g/1000 mL; POTASSIUM PHOSPHATE, MONOBASIC 0.5 g/1000 mL; SODIUM CHLORIDE 2.0 g/1000 mL

AMCALCILYTE FORTE

INDICATIONS AND USAGE

Oral Solution

Calcium and Electrolytes Fortified with Dextrose and Crystalline Amino Acids

For Animal Use Only

KEEP OUT OF REACH OF CHILDREN

INDICATIONS

For use as a supplemental nutritive source of electolytes, dextrose and amino acids in cattle.

DOSAGE AND ADMINISTRATION

Administer orally as a drench. The usual recommended dose in adult cattle is 500 to 1000 mL, depending on size and condition.

STORAGE AND HANDLING

Store at controlled room temperature between 15° and 30°C (59°-86°F)

TAKE TIME OBSERVE LABEL DIRECTIONS

COMPOSITION

Each 1000 mL of aqueous solution contains:

Dextrose • H2O ....................................... 275.0 g
Calcium Hypophosphite ............................ 36.5 g
Potassium Chloride .................................. 15.0 g
Sodium Chloride ........................................ 2.0 g
Potassium Phosphate, monobasic ............... 0.5 g

Comprised of: L-Glutamic Acid, L-Arginine Hydrochloride, L-Proline, L-Lysine Hydrochloride, L-Leuicne, L-Phenylalanine, L-Valine, L-Threonine, L-Isoleucine, L-Histidine Hydrochloride, L-Metionine, L-Tyrosine, with Methylparaben (preservative) 0.09%, Propylparaben (preservative)0.01%